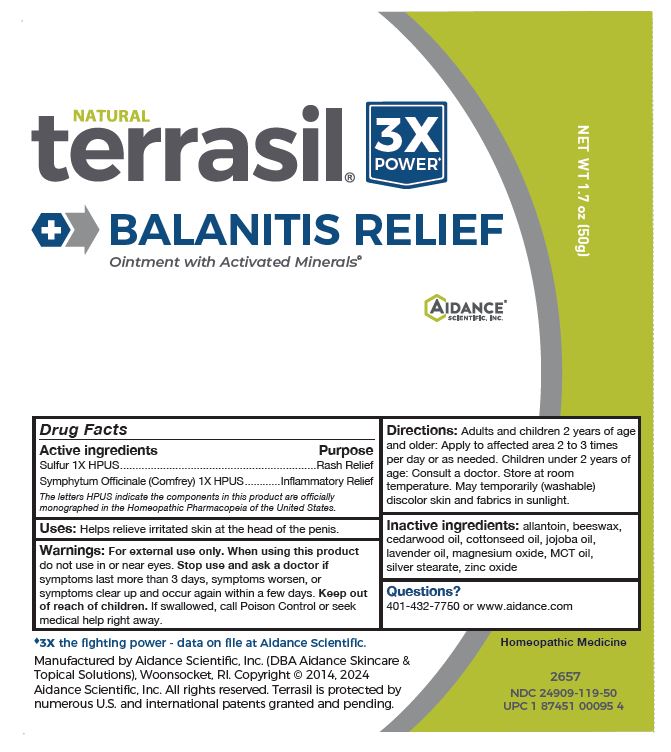 DRUG LABEL: Terrasil Balanitis Relief
NDC: 24909-119 | Form: OINTMENT
Manufacturer: Aidance Scientific, Inc., DBA Aidance Skincare & Topical Solutions
Category: homeopathic | Type: HUMAN OTC DRUG LABEL
Date: 20241120

ACTIVE INGREDIENTS: SULFUR 1 [hp_X]/1 g; SYMPHYTUM OFFICINALE WHOLE 1 [hp_X]/1 g
INACTIVE INGREDIENTS: ALLANTOIN; CEDRUS ATLANTICA BARK OIL; MEDIUM-CHAIN TRIGLYCERIDES; COTTONSEED OIL; JOJOBA OIL; LAVENDER OIL; MAGNESIUM OXIDE; SILVER STEARATE; WHITE WAX; ZINC OXIDE

24909-119 terrasil Balanitis Relief Ointment

Active Ingredient

Sulfur 1X HPUS
Symphytum Officinale (Comfrey) 1X HPUS

Purpose

Sulfur - Rash Relief
Symphytum Officinale - Inflammatory Relief

Uses

Helps relieve irritated skin at the head of the penis.

Warnings

For external use only. When using this product do not use in or near eyes. Stop use and ask a doctor if symptoms last more than 3 days, symptoms worsen, or symptoms clear up and occur again within a few days.

Keep out of reach of children. If swallowed, call Poison Control or seek medical help right away.

Directions

Adults and children 2 years of age and older: Apply to affected area 2 to 3 times per day or as needed. Children under 2 years of age: Consult a doctor. Store at room temperature. May temporarily (washable) discolor skin and fabrics in sunlight.

Inactive Ingredients

allantoin, beeswax, cedarwood oil, cottonseed oil, jojoba oil, lavender oil, magnesium oxide, MCT Oil, silver stearate, zinc oxide.